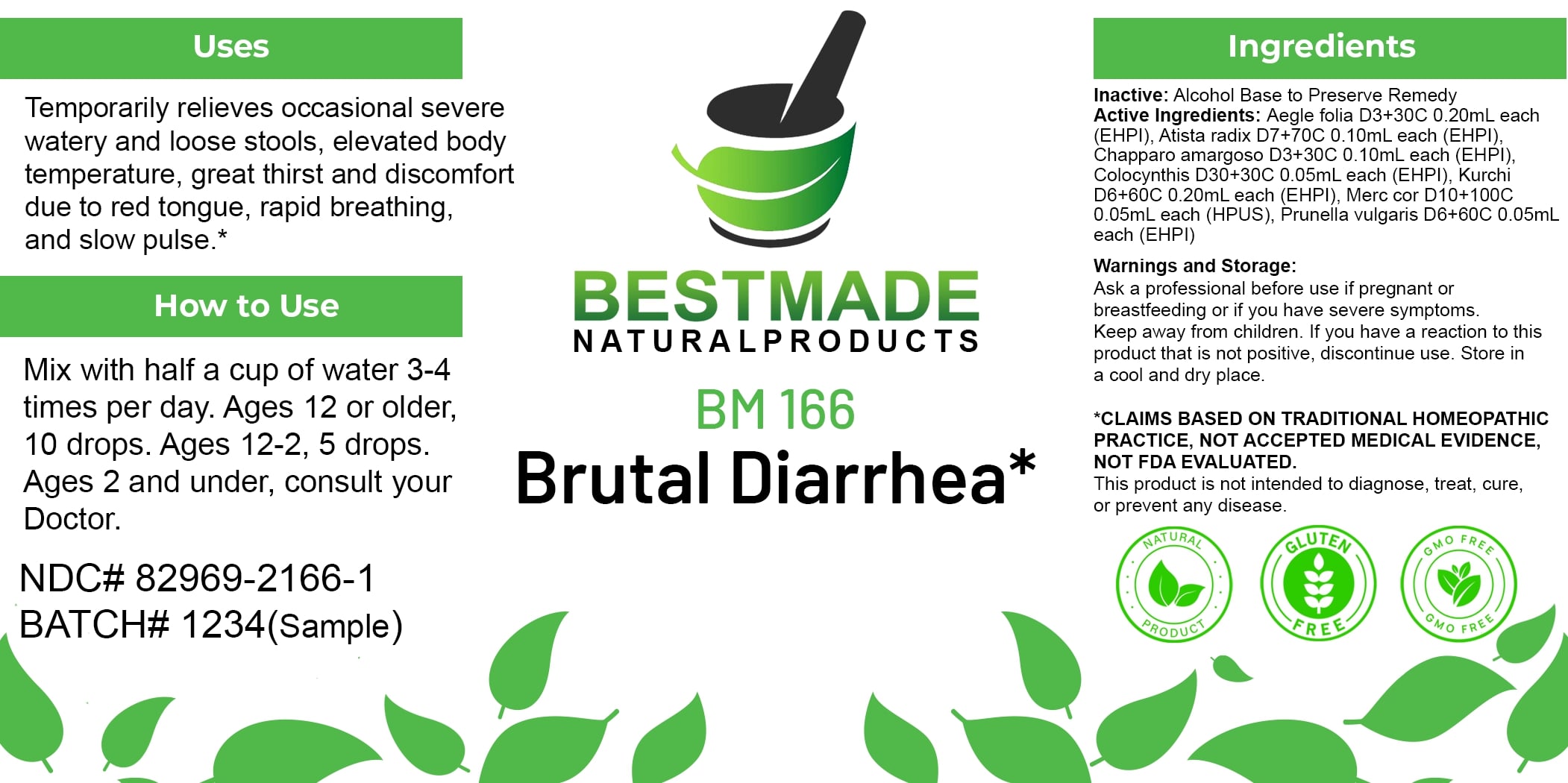 DRUG LABEL: Bestmade Natural Products BM166
NDC: 82969-2166 | Form: LIQUID
Manufacturer: Bestmade Natural Products
Category: homeopathic | Type: HUMAN OTC DRUG LABEL
Date: 20250219

ACTIVE INGREDIENTS: HOLARRHENA PUBESCENS BARK 30 [hp_C]/30 [hp_C]; PRUNELLA VULGARIS 30 [hp_C]/30 [hp_C]; AEGLE MARMELOS LEAF 30 [hp_C]/30 [hp_C]; MERCURIC CHLORIDE 30 [hp_C]/30 [hp_C]; ARISTOLOCHIA DEBILIS ROOT 30 [hp_C]/30 [hp_C]; CASTELA EMORYI WHOLE 30 [hp_C]/30 [hp_C]; CITRULLUS COLOCYNTHIS FRUIT PULP 30 [hp_C]/30 [hp_C]
INACTIVE INGREDIENTS: ALCOHOL 30 [hp_C]/30 [hp_C]

BM166

DOSAGE AND ADMINISTRATION

How to Use
Mix with half a cup of water 3-4 times per day. Ages 12 or older, 10 drops. Ages 2-12, 5 drops. Ages 2 and under, consult your Doctor.

INACTIVE INGREDIENT

Ingredients
Inactive: Alcohol Base to Preserve Remedy

ACTIVE INGREDIENT

Active Ingredients: Aegle folia D3+30C 0.20mL each (EHPI), Atista radix D7+70C 0.10mL each (EHPI), Chapparo amargoso D3+30C 0.10mL each (EHPI), Colocynthis D30+30C 0.05mL each (EHPI), Kurchi D6+60C 0.20mL each (EHPI), Merc cor D10+100C 0.05mL each (HPUS), Prunella vulgaris D6+60C 0.05mL each (EHPI)

Uses
Temporarily relieves occasional severe watery and loose stools, elevated body temperature, great thirst and discomfort due to red tongue, rapid breathing, and slow pulse.*

*CLAIMS BASED ON TRADITIONAL HOMEOPATHIC PRACTICE, NOT ACCEPTED MEDICAL EVIDENCE, NOT FDA EVALUATED.
This product is not intended to diagnose, treat, cure, or prevent any disease.

Uses
Temporarily relieves occasional severe watery and loose stools, elevated body temperature, great thirst and discomfort due to red tongue, rapid breathing, and slow pulse.*

*CLAIMS BASED ON TRADITIONAL HOMEOPATHIC PRACTICE, NOT ACCEPTED MEDICAL EVIDENCE, NOT FDA EVALUATED.
This product is not intended to diagnose, treat, cure, or prevent any disease.

KEEP OUT OF REACH OF CHILDREN

Warnings and Storage:
Ask a professional before use if pregnant or breastfeeding or if you have severe symptoms.
Keep away from children. If you have a reaction to this product that is not positive, discontinue use. Store in a cool and dry place.

Warnings and Storage:
Ask a professional before use if pregnant or breastfeeding or if you have severe symptoms.
Keep away from children. If you have a reaction to this product that is not positive, discontinue use. Store in a cool and dry place.

*CLAIMS BASED ON TRADITIONAL HOMEOPATHIC PRACTICE, NOT ACCEPTED MEDICAL EVIDENCE, NOT FDA EVALUATED.
This product is not intended to diagnose, treat, cure, or prevent any disease.

Entire package label